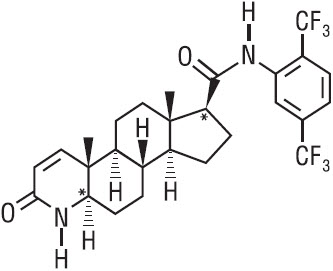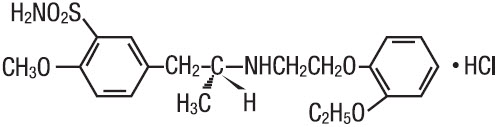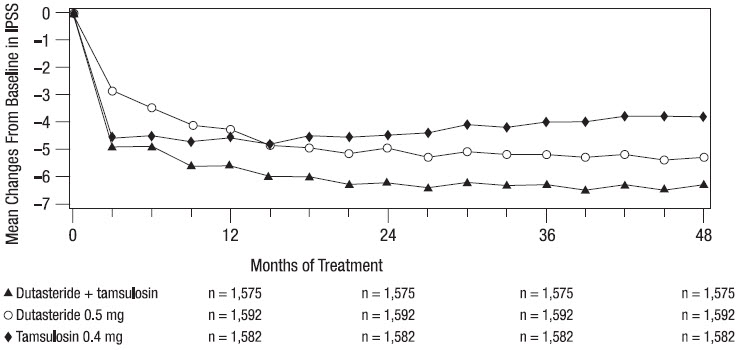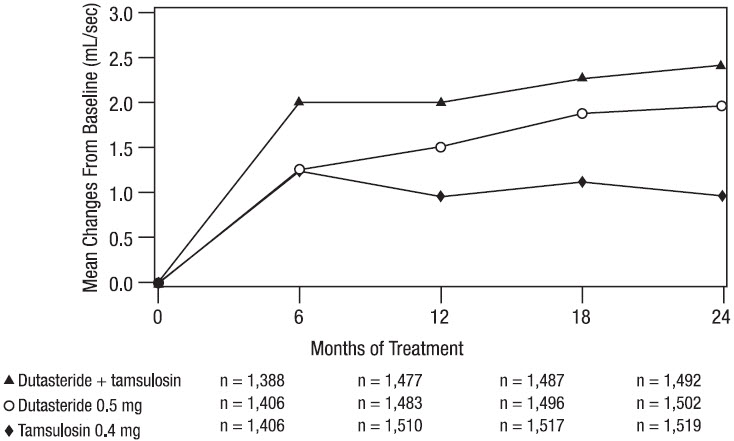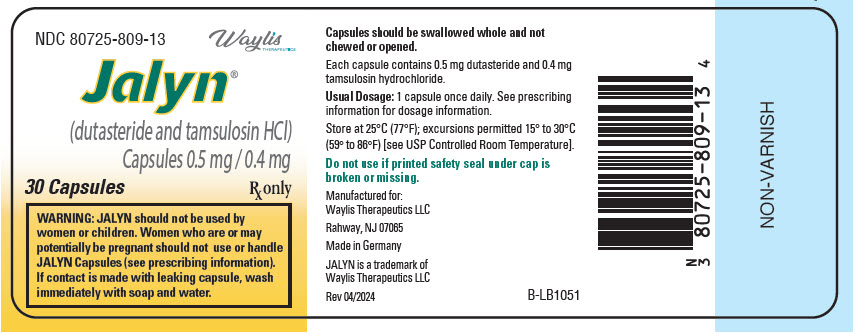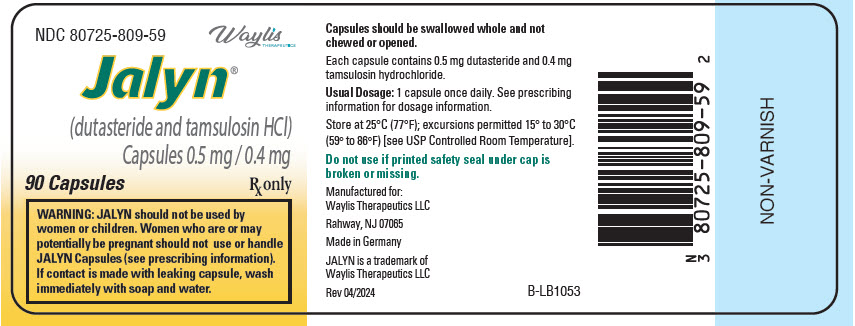 DRUG LABEL: Jalyn
NDC: 80725-809 | Form: CAPSULE
Manufacturer: Waylis Therapeutics
Category: prescription | Type: HUMAN PRESCRIPTION DRUG LABEL
Date: 20240718

ACTIVE INGREDIENTS: DUTASTERIDE 0.5 mg/1 1; TAMSULOSIN HYDROCHLORIDE 0.4 mg/1 1
INACTIVE INGREDIENTS: METHACRYLIC ACID AND ETHYL ACRYLATE COPOLYMER; microcrystalline cellulose; Talc; triethyl citrate

HIGHLIGHTS OF PRESCRIBING INFORMATION

These highlights do not include all the information needed to use JALYN safely and effectively. See full prescribing information for JALYN.
JALYN (dutasteride and tamsulosin hydrochloride) capsules
Initial U.S. Approval: 2010

RECENT MAJOR CHANGES

Contraindications (4) | 12/2020

1 INDICATIONS AND USAGE

JALYN is a combination of dutasteride, a 5-alpha-reductase inhibitor, and tamsulosin, an alpha-adrenergic antagonist, indicated for the treatment of symptomatic benign prostatic hyperplasia (BPH) in men with an enlarged prostate. (1.1)

Limitations of Use: Dutasteride-containing products, including JALYN, are not approved for the prevention of prostate cancer. (1.2)

2 DOSAGE AND ADMINISTRATION

- Take one capsule daily approximately 30 minutes after the same meal each day.(2)
- Swallow capsule whole. (2)

3 DOSAGE FORMS AND STRENGTHS

0.5 mg dutasteride and 0.4 mg tamsulosin hydrochloride. (3)

4 CONTRAINDICATIONS

- Pregnancy. Dutasteride use is contraindicated in females who are pregnant. (4, 5.6, 8.1)
- Patients with previously demonstrated, clinically significant hypersensitivity (e.g., serious skin reactions, angioedema, urticaria, pruritus, respiratory symptoms) to dutasteride, other 5-alpha-reductase inhibitors, tamsulosin, or any component of JALYN. (4)

5 WARNINGS AND PRECAUTIONS

- Orthostatic hypotension and/or syncope can occur. Advise patients of symptoms related to postural hypotension and to avoid situations where injury could result if syncope occurs. (5.1)
- Do not use JALYN with other alpha-adrenergic antagonists, as this may increase the risk of hypotension. (5.2)
- JALYN reduces serum prostate-specific antigen (PSA) concentration by approximately 50%. However, any confirmed increase in PSA while on JALYN may signal the presence of prostate cancer and should be evaluated, even if those values are still within the normal range for untreated men. (5.3)
- Do not use JALYN with strong inhibitors of cytochrome P450 (CYP) 3A4 (e.g., ketoconazole). Use caution in combination with moderate CYP3A4 inhibitors (e.g., erythromycin) or strong (e.g., paroxetine) or moderate CYP2D6 inhibitors, a combination of both CYP3A4 and CYP2D6 inhibitors, or known poor metabolizers of CYP2D6. Concomitant use with known inhibitors can cause a marked increase in drug exposure. (5.2, 7.1, 12.3)
- Exercise caution with concomitant use of phosphodiesterase-5 (PDE-5) inhibitors, as this may increase the risk of hypotension. (5.2)
- Drugs that contain dutasteride, including JALYN, may increase the risk of high-grade prostate cancer. (5.4, 6.1)
- Prior to initiating treatment with JALYN, consideration should be given to other urological conditions that may cause similar symptoms. (5.5)
- Females who are pregnant or may be pregnant should not handle JALYN capsules due to potential risk to a male fetus. (5.6, 8.1)
- Advise patients about the possibility and seriousness of priapism. (5.7)
- Patients should not donate blood until 6 months after their last dose of JALYN. (5.8)
- Intraoperative Floppy Iris Syndrome has been observed during cataract and glaucoma surgery after alpha-adrenergic antagonist exposure. Advise patients considering cataract or glaucoma surgery to tell their ophthalmologist that they take or have taken JALYN capsules. (5.9)
- Exercise caution with concomitant use of warfarin. (5.2, 7.2, 12.3)

6 ADVERSE REACTIONS

The most common adverse reactions, reported in ≥1% of subjects treated with coadministered dutasteride and tamsulosin are ejaculation disorders, impotence, decreased libido, dizziness, and breast disorders. (6.1)

To report SUSPECTED ADVERSE REACTIONS, contact Waylis Therapeutics LLC at 1-844-200-7910 or FDA at 1-800-FDA-1088 or www.fda.gov/medwatch.

FULL PRESCRIBING INFORMATION

1 INDICATIONS AND USAGE

1.1 Benign Prostatic Hyperplasia (BPH) Treatment

JALYN (dutasteride and tamsulosin hydrochloride) capsules are indicated for the treatment of symptomatic BPH in men with an enlarged prostate.

1.2 Limitations of Use

Dutasteride-containing products, including JALYN, are not approved for the prevention of prostate cancer.

2 DOSAGE AND ADMINISTRATION

The recommended dosage of JALYN is 1 capsule (0.5 mg dutasteride and 0.4 mg tamsulosin hydrochloride) taken once daily approximately 30 minutes after the same meal each day.

The capsules should be swallowed whole and not chewed or opened. Contact with the contents of the JALYN capsule may result in irritation of the oropharyngeal mucosa.

3 DOSAGE FORMS AND STRENGTHS

JALYN capsules, containing 0.5 mg dutasteride and 0.4 mg tamsulosin hydrochloride, are oblong, hard-shell capsules with a brown body and an orange cap imprinted with "GS 7CZ" in black ink.

4 CONTRAINDICATIONS

JALYN is contraindicated for use in:

- Pregnancy. Dutasteride use is contraindicated in females who are pregnant.
  In animal reproduction and developmental toxicity studies, dutasteride inhibited development of male fetus external genitalia. Therefore, JALYN may cause fetal harm when administered to a pregnant female [see Warnings and Precautions (5.6), Use in Specific Populations (8.1)].
- Patients with previously demonstrated, clinically significant hypersensitivity (e.g., serious skin reactions, angioedema, urticaria, pruritus, respiratory symptoms) to dutasteride, other 5-alpha-reductase inhibitors, tamsulosin, or any other component of JALYN [see Adverse Reactions (6.2)].

5 WARNINGS AND PRECAUTIONS

5.1 Orthostatic Hypotension

As with other alpha-adrenergic antagonists, orthostatic hypotension (postural hypotension, dizziness, and vertigo) may occur in patients treated with tamsulosin-containing products, including JALYN, and can result in syncope. Patients starting treatment with JALYN should be cautioned to avoid situations where syncope could result in an injury [see Adverse Reactions (6.1)].

5.2 Drug-Drug Interactions

Strong Inhibitors of Cytochrome P450 (CYP) 3A4

Tamsulosin-containing products, including JALYN, should not be coadministered with strong CYP3A4 inhibitors (e.g., ketoconazole) as this can significantly increase tamsulosin exposure [see Drug Interactions (7.1), Clinical Pharmacology (12.3)].

Moderate Inhibitors of CYP3A4, Inhibitors of CYP2D6, or a Combination of Both CYP3A4 and CYP2D6 Inhibitors

Tamsulosin-containing products, including JALYN, should be used with caution when coadministered with moderate inhibitors of CYP3A4 (e.g., erythromycin), strong (e.g., paroxetine) or moderate (e.g., terbinafine) inhibitors of CYP2D6, a combination of both CYP3A4 and CYP2D6 inhibitors, or in patients known to be poor metabolizers of CYP2D6, as there is a potential for significant increase in tamsulosin exposure [see Drug Interactions (7.1), Clinical Pharmacology (12.3)].

Cimetidine

Caution is advised when tamsulosin-containing products, including JALYN, are coadministered with cimetidine [see Drug Interactions (7.1), Clinical Pharmacology (12.3)].

Other Alpha-adrenergic Antagonists

Tamsulosin-containing products, including JALYN, should not be coadministered with other alpha-adrenergic antagonists because of the increased risk of symptomatic hypotension.

Phosphodiesterase-5 (PDE-5) Inhibitors

Caution is advised when alpha-adrenergic–antagonist-containing products, including JALYN, are coadministered with PDE-5 inhibitors. Alpha-adrenergic antagonists and PDE-5 inhibitors are both vasodilators that can lower blood pressure. Concomitant use of these 2 drug classes can potentially cause symptomatic hypotension.

Warfarin

Caution should be exercised with concomitant administration of warfarin and tamsulosin-containing products, including JALYN [see Drug Interactions (7.2), Clinical Pharmacology (12.3)].

5.3 Effects on Prostate-Specific Antigen (PSA) and the Use of PSA in Prostate Cancer Detection

Coadministration of dutasteride with tamsulosin resulted in similar changes to serum PSA as with dutasteride monotherapy.

In clinical trials, dutasteride reduced serum PSA concentration by approximately 50% within 3 to 6 months of treatment. This decrease was predictable over the entire range of PSA values in patients with symptomatic BPH, although it may vary in individuals. Dutasteride-containing treatment, including JALYN, may also cause decreases in serum PSA in the presence of prostate cancer. To interpret serial PSAs in men treated with a dutasteride-containing product, including JALYN, a new baseline PSA should be established at least 3 months after starting treatment and PSA monitored periodically thereafter. Any confirmed increase from the lowest PSA value while on a dutasteride-containing treatment, including JALYN, may signal the presence of prostate cancer and should be evaluated, even if PSA levels are still within the normal range for men not taking a 5-alpha-reductase inhibitor. Noncompliance with JALYN may also affect PSA test results.

To interpret an isolated PSA value in a man treated with JALYN, for 3 months or more, the PSA value should be doubled for comparison with normal values in untreated men.

The free-to-total PSA ratio (percent free PSA) remains constant, even under the influence of dutasteride. If clinicians elect to use percent free PSA as an aid in the detection of prostate cancer in men receiving JALYN, no adjustment to its value appears necessary.

5.4 Increased Risk of High-Grade Prostate Cancer

In men aged 50 to 75 years with a prior negative biopsy for prostate cancer and a baseline PSA between 2.5 ng/mL and 10.0 ng/mL taking dutasteride in the 4-year Reduction by Dutasteride of Prostate Cancer Events (REDUCE) trial, there was an increased incidence of Gleason score 8 to 10 prostate cancer compared with men taking placebo (dutasteride 1.0% versus placebo 0.5%) [see Indications and Usage

5.5 Evaluation for Other Urological Diseases

Prior to initiating treatment with JALYN, consideration should be given to other urological conditions that may cause similar symptoms. In addition, BPH and prostate cancer may coexist.

5.6 Transdermal Exposure of JALYN in Pregnant Females—Risk to Male Fetus

JALYN capsules should not be handled by females who are pregnant or may be pregnant. Dutasteride can be absorbed through the skin and could result in unintended fetal exposure and potential risk to a male fetus. If a female who is or may be pregnant comes in contact with a leaking capsule, the contact area should be washed immediately with soap and water [see Use in Specific Populations (8.1)]. Dutasteride can be absorbed through the skin based on animal studies [see Nonclinical Toxicology (13.2)].

5.7 Priapism

Priapism (persistent painful penile erection unrelated to sexual activity) has been associated (probably less than 1 in 50,000) with the use of alpha-adrenergic antagonists, including tamsulosin, which is a component of JALYN. Because this condition can lead to permanent impotence if not properly treated, patients should be advised about the seriousness of the condition.

5.8 Blood Donation

Men being treated with a dutasteride-containing product, including JALYN, should not donate blood until at least 6 months have passed following their last dose.

The purpose of this deferred period is to prevent administration of dutasteride to a pregnant female transfusion recipient.

5.9 Intraoperative Floppy Iris Syndrome

Intraoperative Floppy Iris Syndrome (IFIS) has been observed during cataract and glaucoma surgery in some patients on or previously treated with alpha-adrenergic antagonists, including tamsulosin, which is a component of JALYN.

Most reports were in patients taking the alpha-adrenergic antagonist when IFIS occurred, but in some cases, the alpha-adrenergic antagonist had been stopped prior to surgery. In most of these cases, the alpha-adrenergic antagonist had been stopped recently prior to surgery (2 to 14 days), but in a few cases, IFIS was reported after the patients had been off the alpha-adrenergic antagonist for a longer period (5 weeks to 9 months). IFIS is a variant of small pupil syndrome and is characterized by the combination of a flaccid iris that billows in response to intraoperative irrigation currents, progressive intraoperative miosis despite preoperative dilation with standard mydriatic drugs, and potential prolapse of the iris toward the phacoemulsification incisions. The patient's ophthalmologist should be prepared for possible modifications to their surgical technique, such as the utilization of iris hooks, iris dilator rings, or viscoelastic substances.

IFIS may increase the risk of eye complications during and after the operation.

The benefit of stopping alpha-adrenergic antagonist therapy prior to cataract or glaucoma surgery has not been established. The initiation of therapy with tamsulosin in patients for whom cataract or glaucoma surgery is scheduled is not recommended.

5.10 Sulfa Allergy

In patients with sulfa allergy, allergic reaction to tamsulosin has been rarely reported.

If a patient reports a serious or life-threatening sulfa allergy, caution is warranted when administering tamsulosin-containing products, including JALYN.

5.11 Effect on Semen Characteristics

Dutasteride

The effects of dutasteride 0.5 mg/day on semen characteristics were evaluated in healthy men throughout 52 weeks of treatment and 24 weeks of post-treatment follow-up. At 52 weeks, compared wıth placebo, dutasteride treatment resulted in mean reduction in total sperm count, semen volume, and sperm motility; the effects on total sperm count were not reversible after 24 weeks of follow-up. Sperm concentration and sperm morphology were unaffected and mean values for all semen parameters remained within the normal range at all timepoints. The clinical significance of the effect of dutasteride on semen characteristics for an individual patient's fertility is not known [see Use in Specific Populations (8.3)].

Tamsulosin

The effects of tamsulosin hydrochloride on sperm counts or sperm function have not been evaluated.

6 ADVERSE REACTIONS

6.1 Clinical Trials Experience

The clinical efficacy and safety of coadministered dutasteride and tamsulosin, which are individual components of JALYN, have been evaluated in a multicenter, randomized, double-blind, parallel group trial (the Combination with Alpha-Blocker Therapy, or CombAT, trial). Because clinical trials are conducted under widely varying conditions, adverse reaction rates observed in the clinical trials of a drug cannot be directly compared with rates in the clinical trial of another drug and may not reflect the rates observed in practice.

- The most common adverse reactions reported in subjects receiving coadministered dutasteride and tamsulosin were impotence, decreased libido, breast disorders (including breast enlargement and tenderness), ejaculation disorders, and dizziness. Ejaculation disorders occurred significantly more in subjects receiving coadministration therapy (11%) compared with those receiving dutasteride (2%) or tamsulosin (4%) as monotherapy.
- Trial withdrawal due to adverse reactions occurred in 6% of subjects receiving coadministered dutasteride and tamsulosin and in 4% of subjects receiving dutasteride or tamsulosin as monotherapy. The most common adverse reaction in all treatment arms leading to trial withdrawal was erectile dysfunction (1% to 1.5%).

In the CombAT trial, over 4,800 male subjects with BPH were randomly assigned to receive 0.5 mg dutasteride, 0.4 mg tamsulosin hydrochloride, or coadmınistration therapy (0.5 mg dutasteride and 0.4 mg tamsulosin hydrochloride) administered once daily in a 4-year double-blind trial. Overall, 1,623 subjects received monotherapy with dutasteride; 1,611 subjects received monotherapy with tamsulosin; and 1,610 subjects received coadministration therapy. The population was aged 49 to 88 years (mean age: 66 years) and 88% were white. Table 1 summarizes adverse reactions reported in at least 1% of subjects receiving coadministration therapy and at a higher incidence than subjects receiving either dutasteride or tamsulosin as monotherapy.

Table 1. Adverse Reactions Reported over a 48-Month Period in ≥1% of Subjects and More Frequently in the Coadministration Therapy Group than the Dutasteride or Tamsulosin Monotherapy Group (CombAT) by Time of Onset
Adverse Reaction | Adverse Reaction Time of Onset
Adverse Reaction | Year 1 |  | Year 2 | Year 3 | Year 4
Adverse Reaction | Months 0-6 | Months 7-12 | Year 2 | Year 3 | Year 4
Coadministration [Coadministration − AVODART 0.5 mg once daily plus tamsulosin 0.4 mg once daily.] | (n = 1,610) | (n = 1,527) | Year 2 | Year 3 | Year 4 | (n = 1,428) | (n = 1,283) | (n = 1,200)
Dutasteride | (n = 1,623) | (n = 1,548) | (n = 1,464) | (n = 1,325) | (n = 1,200)
Tamsulosin | (n = 1,611) | (n = 1,545) | (n = 1,468) | (n = 1,281) | (n = 1,112)
Ejaculation disorders [Includes anorgasmia, retrograde ejaculation, semen volume decreased, orgasmic sensation decreased, orgasm abnormal, ejaculation delayed, ejaculation disorder, ejaculation failure, and premature ejaculation.] , [These sexual adverse reactions are associated with dutasteride treatment (including monotherapy and combination with tamsulosin). These adverse reactions may persist after treatment discontinuation. The role of dutasteride in this persistence is unknown.]
Coadministration | 7.8% | 1.6% | 1.0% | 0.5% | <0.1%
Dutasteride | 1.0% | 0.5% | 0.5% | 0.2% | 0.3%
Tamsulosin | 2.2% | 0.5% | 0.5% | 0.2% | 0.3%
Impotence, [Includes erectile dysfunction and disturbance in sexual arousal.]
Coadministration | 5.4% | 1.1% | 1.8% | 0.9% | 0.4%
Dutasteride | 4.0% | 1.1% | 1.6% | 0.6% | 0.3%
Tamsulosin | 2.6% | 0.8% | 1.0% | 0.6% | 1.1%
Decreased libido, [Includes libido decreased, libido disorder, loss of libido, sexual dysfunction, and male sexual dysfunction.]
Coadministration | 4.5% | 0.9% | 0.8% | 0.2% | 0.0%
Dutasteride | 3.1% | 0.7% | 1.0% | 0.2% | 0.0%
Tamsulosin | 2.0% | 0.6% | 0.7% | 0.2% | <0.1%
Breast disorders [Includes breast enlargement, gynecomastia, breast swelling, breast pain, breast tenderness, nipple pain, and nipple swelling.]
Coadministration | 1.1% | 1.1% | 0.8% | 0.9% | 0.6%
Dutasteride | 0.9% | 0.9% | 1.2% | 0.5% | 0.7%
Tamsulosin | 0.4% | 0.4% | 0.4% | 0.2% | 0.0%
Dizziness
Coadministration | 1.1% | 0.4% | 0.1% | <0.1% | 0.2%
Dutasteride | 0.5% | 0.3% | 0.1% | <0.1% | <0.1%
Tamsulosin | 0.9% | 0.5% | 0.4% | <0.1% | 0.0%

Cardiac Failure

In CombAT, after 4 years of treatment, the incidence of the composite term cardiac failure in the coadministration group (12/1,610; 0.7%) was higher than in either monotherapy group: dutasteride, 2/1,623 (0.1%) and tamsulosin, 9/1,611 (0.6%). Composite cardiac failure was also examined in a separate 4-year placebo-controlled trial evaluating dutasteride in men at risk for development of prostate cancer.

The incidence of cardiac failure in subjects taking dutasteride was 0.6% (26/4,105) compared with 0.4% (15/4,126) in subjects on placebo. A majority of subjects with cardiac failure in both trials had comorbidities associated with an increased risk of cardiac failure. Therefore, the clinical significance of the numerical imbalances in cardiac failure is unknown. No causal relationship between dutasteride alone or coadministered with tamsulosin and cardiac failure has been established.

No imbalance was observed in the incıdence of overall cardiovascular adverse events in either trial.

Additional information regarding adverse reactions in placebo-controlled trials with dutasteride or tamsulosin monotherapy follows.

Dutasteride

Long-term Treatment (Up to 4 Years): High-Grade Prostate Cancer: The REDUCE trial was a randomized, double-blind, placebo-controlled trial that enrolled 8,231 men aged 50 to 75 years with a serum PSA of 2.5 ng/mL to 10 ng/mL and a negative prostate biopsy within the previous. 6 months. Subjects were randomized to receive placebo (n = 4,126) or 0.5-mg daily doses of dutasteride (n = 4,105) for up to 4 years. The mean age was 63 years and 91% were white. Subjects underwent protocol-mandated scheduled prostate biopsies at 2 and 4 years of treatment or had "for-cause biopsies" at non-scheduled times if clinically indicated. There was a higher incidence of Gleason score 8 to 10 prostate cancer in men receiving dutasteride (1.0%) compared with men on placebo (0.5%) [see Indications and Usage (1.2), Warnings and Precautions (5.4)]. In a 7-year placebo-controlled clinical trial with another 5-alpha-reductase inhibitor (finasteride 5 mg, PROSCAR), similar results for Gleason score 8 to 10 prostate cancer were observed (finasteride 1.8% versus placebo 1.1%).

No clinical benefit has been demonstrated in patients with prostate cancer treated with dutasteride.

Reproductive and Breast Disorders

In the 3 pivotal placebo-controlled BPH trials with dutasteride, each 4 years in duration, there was no evidence of increased sexual adverse reactions (impotence, decreased libido, and ejaculation disorder) or breast disorders with increased duration of treatment. Among these 3 trials, there was 1 case of breast cancer in the dutasteride group and 1 case in the placebo group. No cases of breast cancer were reported in any treatment group in the 4-year CombAT trial or the 4-year REDUCE trial. The relationship between long-term use of dutasteride and male breast neoplasia is currently unknown.

Tamsulosin

According to the tamsulosin prescribing information, in two 13-week treatment trials with tamsulosin monotherapy, adverse reactions occurring in at least 2% of subjects receiving 0.4 mg tamsulosin hydrochloride and at an incidence higher than in subjects receiving placebo were: infection, asthenia, back pain, chest pain, somnolence, insomnia, rhinitis, pharyngitis, cough increased, sinusitis, and diarrhea.

Signs and Symptoms of Orthostasis: According to the tamsulosin prescribing information, in clinical trials with tamsulosin monotherapy, a positive orthostatic test result was observed in 16% (81/502) of subjects receivıng 0.4 mg tamsulosin hydrochloride versus 11% (54/493) of subjects receiving placebo. Because orthostasis was detected more frequently in the tamsulosin-treated subjects than in placebo recipients, there is a potential risk of syncope [see Warnings and Precautions (5.1)].

6.2 Postmarketing Experience

The following adverse reactions have been identified during postapproval use of the individual components of JALYN. Because these reactions are reported voluntarily from a population of uncertain size, it is not always possible to reliably estimate their frequency or establish a causal relationship to drug exposure. These reactions have been chosen for inclusion due to a combination of their seriousness, frequency of reporting, or potential causal connection to drug exposure.

Dutasteride

Immune System Disorders: Hypersensitivity reactions, including rash, pruritus, urticaria, localized edema, serious skin reactions, and angioedema.

Neoplasms: Male breast cancer.

Psychiatric Disorders: Depressed mood.

Reproductive System and Breast Disorders: Testicular pain and testicular swelling.

Tamsulosin

Immune System Disorders: Hypersensitivity reactions, including rash, urticaria, pruritus, angioedema, and respiratory problems have been reported with positive rechallenge in some cases.

Cardiac Disorders: Palpitations, dyspnea, atrial fibrillation, arrhythmia, and tachycardia.

Skin Disorders: Skin desquamation, including Stevens-Johnson syndrome, erythema multiforme, dermatitis exfoliative.

Gastrointestinal Disorders: Constipation, vomiting, dry mouth.

Reproductive System and Breast Disorders: Priapism.

Respiratory: Epistaxis.

Vascular Disorders: Hypotension.

Ophthalmologic Disorders: Blurred vision, visual impairment. During cataract and glaucoma surgery, a variant of small pupil syndrome known as Intraoperative Floppy Iris Syndrome (IFIS) associated with alpha-adrenergic antagonist therapy [see Warnings and Precautions (5.9)].

7 DRUG INTERACTIONS

There have been no drug interaction trials using JALYN. The following sections reflect information available for the individual components.

7.1 Cytochrome P450 Inhibition

Dutasteride

Dutasteride is extensively metabolized in humans by the CYP3A4 and CYP3A5 isoenzymes. The effect of potent CYP3A4 inhibitors on dutasteride has not been studied. Because of the potential for drug-drug interactions, use caution when prescribing a dutasteride-containing product, including JALYN, to patients taking potent, chronic CYP3A4 enzyme inhibitors (e.g., ritonavir) [see Clinical Pharmacology (12.3)]

Tamsulosin

Strong and Moderate Inhibitors of CYP3A4 or CYP2D6: Tamsulosin is extensively metabolized, mainly by CYP3A4 or CYP2D6.

Concomitant treatment with ketoconazole (a strong inhibitor of CYP3A4) resulted in increases in the Cmax and area under the concentration-time curve (AUC) of tamsulosin by factors of 2.2 and 2.8, respectively. Concomitant treatment with paroxetine (a strong inhibitor of CYP2D6) resulted in increases in the Cmax and AUC of tamsulosin by factors of 1.3 and 1.6, respectively. A similar increase in exposure is expected in poor metabolizers (PM) of CYP2D6 as compared to extensive metabolizers (EM). Since CYP2D6 PMs cannot be readily identified and the potential for significant increase in tamsulosin exposure exists when tamsulosin 0.4 mg is coadministered with strong CYP3A4 inhibitors in CYP2D6 PMs, tamsulosin 0.4 mg capsules should not be used in combination wıth strong inhibitors of CYP3A4 (e.g., ketoconazole). The effects of coadministration of both a CYP3A4 and a CYP2D6 inhibitor with tamsulosin have not been evaluated. However, there is a potential for significant increase in tamsulosin exposure when tamsulosin 0.4 mg is coadministered with a combination of both CYP3A4 and CYP2D6 inhibitors [see Warnings and Precautions (5.2), Clinical Pharmacology (12.3)].

Cimetidine: Treatment with cimetidine resulted in a moderate increase in tamsulosin hydrochloride AUC (44%) [see Warnings and Precautions (5.2), Clinical Pharmacology (12.3)].

7.2 Warfarin

Dutasteride

Concomitant administration of dutasteride 0.5 mg/day for 3 weeks with warfarin does not alter the steady-state pharmacokinetics of the S- or R-warfarin isomers or alter the effect of warfarin on prothrombin time [see Clinical Pharmacology (12.3)].

Tamsulosin

A definitive drug-drug interaction trial between tamsulosin hydrochloride and warfarin was not conducted. Results from limited in vitro and in vivo studies are inconclusive. Caution should be exercised with concomitant administration of warfarin and tamsulosin-containing products, including JALYN [see Warnings and Precautions (5.2), Clinical Pharmacology (12.3)].

7.3 Nifedipine, Atenolol, Enalapril

Tamsulosin

Dosage adjustments are not necessary when tamsulosin is administered concomitantly with nifedipine, atenolol, or enalapril [see Clinical Pharmacology (12.3)].

7.4 Digoxin and Theophylline

Dutasteride

Dutasteride does not alter the steady-state pharmacokinetics of digoxin when administered concomitantly at a dose of 0.5 mg/day for 3 weeks [see Clinical Pharmacology (12.3)].

Tamsulosin

Dosage adjustments are not necessary when tamsulosin is administered concomitantly with digoxin or theophylline [see Clinical Pharmacology (12.3)].

7.5 Furosemide

Tamsulosin

Tamsulosin had no effect on the pharmacodynamics (excretion of electrolytes) of furosemide. While furosemide produced an 11% to 12% reduction in tamsulosin hydrochloride Cmax and AUC, these changes are expected to be clinically insignificant and do not require adjustment of the dose of tamsulosin [see Clinical Pharmacology (12.3)].

7.6 Calcium Channel Antagonists

Dutasteride

Coadministration of verapamil or diltiazem decreases dutasteride clearance and leads to increased exposure to dutasteride. The change in dutasteride exposure is not considered to be clinically significant. No dosage adjustment of dutasteride is recommended [see Clinical Pharmacology (12.3)].

7.7 Cholestyramine

Dutasteride

Administration of a single 5-mg dose of dutasteride followed 1 hour later by a 12-g dose of cholestyramine does not affect the relative bioavailability of dutasteride [see Clinical Pharmacology (12.3)].

8 USE IN SPECIFIC POPULATIONS

8.1 Pregnancy

Risk Summary

JALYN is contraindicated for use in pregnancy because it may cause harm to the male fetus [see Contraindications (4)]. JALYN is not indicated for use in females.

Dutasteride, a component of JALYN, is a 5-alpha-reductase inhibitor that prevents conversion of testosterone to dihydrotestosterone (DHT), a hormone necessary for normal development of male genitalia. Abnormalities in the genitalia of male fetuses is an expected physiological consequence of inhibition of this conversion. These results are similar to observations in male infants with genetic 5-alpha-reductase deficiency.

In animal reproduction studies, dutasteride inhibited normal development of external genitalia in male offspring when given to rats or rabbits during organogenesis at less than the maximum recommended human dose (MRHD) of 0.5 mg daily, in the absence of maternal toxicity. At 15 times the MRHD, prolonged pregnancy, decreased reproductive organ weights, and delayed puberty in male offspring were observed in rats, with no-effect levels less than the MRHD of 0.5 mg daily. Increased placental weights in rabbits were also observed, with no-effect levels less than the MRHD of 0.5 mg daily (see Data).

Although dutasteride is secreted into human semen, the drug concentration in the human female partner is approximately 100 times less than concentrations producing abnormalities of male genitalia in animal studies (see Data). In monkeys dosed during organogenesis at blood concentrations comparable to or above levels to which a human female partner is estimated to be exposed, male offspring external genitalia was not adversely affected. No feminization occurred in male offspring of untreated female rats mated to treated male rats even though detectable blood levels of dutasteride were observed in the female rats [see Nonclinical Toxicology (13.1)].

No adverse developmental effects were observed in animal studies in which tamsulosin hydrochloride was administered to rats or rabbits during the period of organogenesis (see Data).

Data

Human Data: Dutasteride: The highest measured semen concentration of dutasteride in treated men was 14 ng/mL. Although dutasteride is detected in semen, assuming exposure of a 50-kg female to 5 mL of semen and 100% absorption, the female's expected dutasteride blood concentration through semen would be about 0.0175 ng/mL. This concentration is approximately 100 times less than blood concentrations producing abnormalities of male genitalia in animal studies. Dutasteride is highly protein bound in human semen (greater than 96%), which may reduce the amount of dutasteride available for vaginal absorption.

Animal Data: Dutasteride: In an embryo-fetal development study in rats, oral administration of dutasteride at 10 times less than the MRHD of 0.5 mg daily (based on average blood levels in men) resulted in feminization of male genitalia in the fetus (decreased anogenital distance at 0.05 mg/kg/day with a lack of a no-effect level) in the absence of maternal toxicity. In addition, nipple development, hypospadias, and distended preputial glands occurred in fetuses of dams treated at doses of 2.5 mg/kg/day or greater (approximately 15 times the MRHD). Reduced fetal body weight and associated delayed ossification in the presence of maternal toxicity (decreased body weight gain) were observed at maternal exposure approximately 15 times the MRHD (dose of 2.5 mg/kg/day or greater). An increase in stillborn pups was observed in dams treated at 30 mg/kg/day (approximately 111 times the MRHD), with a no-effect level of 12.5 mg/kg/day.

In a rabbit embryo-fetal development study, doses 28 times the MRHD (doses of 30 mg/kg/day or greater), based on average blood levels in men, were administered orally on Gestation Days 7 to 29 (during organogenesis and the late period of external genitalia development). Histological evaluation of the genital papilla of fetuses revealed evidence of feminization of the male fetus as well as fused skull bones and increased placental weights at all doses in the absence of maternal toxicity. A second embryo-fetal development study in rabbits dosed throughout pregnancy (organogenesis and later period of external genitalia development [Gestation Days 6 to 29]) at 0.3 times the MRHD (doses of 0.05 mg/kg/day or greater, with no no-effect level), also produced evidence of feminization of the genitalia in male fetuses and increased placental weights at all doses in the absence of maternal toxicity.

In an embryo-fetal development study, pregnant rhesus monkeys were exposed intravenously during organogenesis (Gestation Days 20 to 100) to a dutasteride blood level comparable to or above the estimated dutasteride exposure of a human female partner. Dutasteride was administered on Gestation Days 20 to 100 (during organogenesis) at doses of 400, 780, 1,325, or 2,010 ng/day (12 monkeys/group). No feminization of male external genitalia of monkey offspring was observed. Reduction of fetal adrenal weights, reduction in fetal prostate weights, and increases in fetal ovarian and testis weights were observed at the highest dose tested. Based on the highest measured semen concentration of dutasteride in treated men (14 ng/mL), these doses in the monkey represent up to 16 times the potential maximum exposure of a 50-kg human female to 5 mL of semen daily from a dutasteride-treated male, assuming 100% absorption. The dose levels (on a ng/kg basis) administered to monkeys in this study are 32 to 186 times the nominal (ng/kg) dose to which a female would potentially be exposed via the semen. It is not known whether rabbits or rhesus monkeys produce any of the major human metabolites.

In an oral pre- and post-natal development study in rats, feminization of the male genitalia was observed. Decreased anogenital distance was observed at 0.05 times the MRHD and greater (0.05 mg/kg/day and greater), with a lack of a no-effect level, based on average blood levels in men as an estimation of AUC. Hypospadias and nipple development were observed at 2.5 mg/kg/day or greater (14 times the MRHD or greater, with a no-effect level at 0.05 mg/kg/day). Doses of 2.5 mg/kg/day and greater also resulted in prolonged gestation in the parental females, an increase in time to balano-preputial separation in male offspring, a decrease in time to vaginal patency for female offspring, and a decrease in prostate and seminal vesicle weights in male offspring. Increased stillbirths and decreased neonatal viability in offspring were noted at 30 mg/kg/day (102 times the MRHD in the presence of maternal toxicity [decreased body weights]).

Tamsulosin: Administration of tamsulosin hydrochloride to pregnant female rats during the period of organogenesis (Gestation Days 7 to 17) at dose levels up to approximately 50 times the human therapeutic AUC exposure (300 mg/kg/day) revealed no evidence of harm to the fetus. Administration of tamsulosin hydrochloride to pregnant rabbits during the period of organogenesis (Gestation Days 6 to 18) at dose levels up to 50 mg/kg/day produced no evidence of fetal harm.

8.2 Lactation

Risk Summary

JALYN is not indicated for use in females.

8.3 Females and Males of Reproductive Potential

Infertility

Dutasteride: Males: The effects of dutasteride 0.5 mg/day on semen characteristics were evaluated in normal volunteers aged 18 to 52 years (n = 27 dutasteride, n = 23 placebo) throughout 52 weeks of treatment and 24 weeks of post-treatment follow-up. At 52 weeks, the mean percent reductions from baseline in total sperm count, semen volume, and sperm motility were 23%, 26%, and 18%, respectively, in the dutasteride group when adjusted for changes from baseline in the placebo group. Sperm concentration and sperm morphology were unaffected. After 24 weeks of follow-up, the mean percent change in total sperm count in the dutasteride group remained 23% lower than baseline. While mean values for all semen parameters at all timepoints remained within the normal ranges and did not meet predefined criteria for a clinically significant change (30%), 2 subjects in the dutasteride group had decreases in sperm count of greater than 90% from baseline at 52 weeks, with partial recovery at the 24-week follow-up. The clinical significance of these effects on semen characteristics for an individual patient's fertility is not known [see Warnings and Precautions (5.11)].

Tamsulosin: Males: Abnormal ejaculation including ejaculation failure, ejaculation disorder, retrograde ejaculation, and decreased ejaculation has been associated with tamsulosin hydrochloride. Studies in rats revealed significantly reduced fertility in males, considered to be due to impairment of ejaculation, which was reversible [see Nonclinical Toxicology (13.1)].

8.4 Pediatric Use

JALYN is not indicated for use in pediatric patients. Safety and effectiveness of JALYN in pediatric patients have not been established.

8.5 Geriatric Use

Of 1,610 male subjects treated with coadministered dutasteride and tamsulosin in the CombAT trial, 58% of enrolled subjects were aged 65 years and older and 13% of enrolled subjects were aged 75 years and older. No overall differences in safety or efficacy were observed between these subjects and younger subjects but greater sensitivity of some older individuals cannot be ruled out [see Clinical Pharmacology (12.3)].

8.6 Renal Impairment

The effect of renal impairment on dutasteride and tamsulosin pharmacokinetics has not been studied using JALYN. Because no dosage adjustment is necessary for dutasteride or tamsulosin in patients with moderate-to-severe renal impairment (10≤ CLcr<30 mL/min/1.73 m2), no dosage adjustment is necessary for JALYN in patients with moderate-to-severe renal impairment. However, patients with end-stage renal disease (CLcr<10 mL/min/1.73 m^2) have not been studied [see Clinical Pharmacology (12.3)].

8.7 Hepatic Impairment

The effect of hepatic impairment on dutasteride and tamsulosin pharmacokinetics has not been studied using JALYN. The following text reflects information available for the individual components.

Dutasteride

The effect of hepatic impairment on dutasteride pharmacokinetics has not been studied. Because dutasteride is extensively metabolized, exposure could be higher in hepatically impaired patients. However, in a clinical trial where 60 subjects received 5 mg (10 times the therapeutic dose) daily for 24 weeks, no additional adverse events were observed compared with those observed at the therapeutıc dose of 0.5 mg [see Clinical Pharmacology (12.3)].

Tamsulosin

Patients with moderate hepatic impairment do not require an adjustment in tamsulosin dosage. Tamsulosin has not been studied in patients with severe hepatic impairment [see Clinical Pharmacology (12.3)].

10 OVERDOSAGE

No data are available with regard to overdosage with JALYN. The following text reflects information available for the individual components.

Dutasteride

In volunteer trials, single doses of dutasteride up to 40 mg (80 times the therapeutic dose) for 7 days have been administered without significant safety concerns. In a clinical trial, daily doses of 5 mg (10 times the therapeutic dose) were administered to 60 subjects for 6 months with no additional adverse effects to those seen at therapeutic doses of 0.5 mg.

There is no specific antidote for dutasteride. Therefore, in cases of suspected overdosage symptomatic and supportive treatment should be given as appropriate, taking the long half-life of dutasteride into consideration.

Tamsulosin

Should overdosage of tamsulosin lead to hypotension [see Warnings and Precautions (5.1), Adverse Reactions (6.1)], support of the cardiovascular system is of first importance. Restoration of blood pressure and normalization of heart rate may be accomplished by keeping the patient in the supine position. If this measure is inadequate, then administration of intravenous fluids should be considered. If necessary, vasopressors should then be used and renal function should be monitored and supported as needed. Laboratory data indicate that tamsulosin is 94% to 99% protein bound; therefore, dialysis is unlikely to be of benefit.

11 DESCRIPTION

JALYN (dutasteride and tamsulosin hydrochloride) capsules contain dutasteride (a selective inhibitor of both the type 1 and type 2 isoforms of steroid 5 alpha-reductase, an intracellular enzyme that converts testosterone to DHT and tamsulosin (an antagonist of alpha1A-adrenoceptors in the prostate). Each JALYN capsule contains the following:

- One dutasteride oblong, opaque, dull-yellow soft gelatin capsule, containing 0.5 mg of dutasteride dissolved in a mixture of butylated hydroxytoluene and mono-di-glycerides of caprylic/capric acid. The inactive ingredients in the soft-gelatin capsule shell are ferric oxide (yellow), gelatin (from certified BSE-free bovine sources), glycerin, and titanium dioxide.
- Tamsulosin hydrochloride white to off-white pellets, containing 0.4 mg tamsulosin hydrochloride and the inactive ingredients: methacrylic acid copolymer dispersion, microcrystalline cellulose, talc, and triethyl citrate.

The above components are encapsulated in a hard-shell capsule made with the inactive ingredients of carrageenan, FD&C yellow 6, hypromellose, iron oxide red, potassium chloride, titanıum dioxide, and imprinted with "GS 7CZ" in black ink.

Dutasteride: Dutasteride is a synthetic 4-azasteroid compound chemically designated as (5α,17β)-N-{2,5 bis(trifluoromethyl)phenyl}-3-oxo-4-azaandrost-1-ene-17-carboxamide. The empirical formula of dutasteride is C27H30F6N2O2, representing a molecular weight of 528.5 with the following structural formula:

Dutasteride is a white to pale yellow powder with a melting point of 242° to 250°C. It is soluble in ethanol (44 mg/mL), methanol (64 mg/mL), and polyethylene glycol 400 (3 mg/mL), but it is insoluble in water.

Tamsulosin: Tamsulosin hydrochloride is a synthetic compound chemically designated as (-)-(R)-5-[2-[[2-(o-Ethoxyphenoxy)ethyl]amino]propyl]-2-methoxybenzenesulfonamide, monohydrochloride.

The empirical formula of tamsulosin hydrochloride is C20H28N2O5S∙HCl. The molecular weight of tamsulosin hydrochloride is 444.97. Its structural formula is:

Tamsulosin hydrochloride is a white or almost white crystalline powder that melts with decomposition at approximately 234°C. It is sparingly soluble in water and slightly soluble in methanol, ethanol, acetone, and ethyl acetate.

12 CLINICAL PHARMACOLOGY

12.1 Mechanism of Action

JALYN is a combination of 2 drugs with different mechanisms of action to improve symptoms in patients with BPH: dutasteride, a 5-alpha-reductase inhibitor, and tamsulosin, an antagonist of alpha1A-adrenoreceptors.

Dutasteride

Dutasteride inhibits the conversion of testosterone to DHT. DHT is the androgen primarily responsible for the initial development and subsequent enlargement of the prostate gland. Testosterone is converted to DHT by the enzyme 5 alpha-reductase, which exists as 2 isoforms, type 1 and type 2. The type 2 isoenzyme is primarily active in the reproductive tissues, while the type 1 isoenzyme is also responsible for testosterone conversion in the skin and liver.

Dutasteride is a competitive and specific inhibitor of both type 1 and type 2 5-alpha-reductase isoenzymes, with which it forms a stable enzyme complex. Dissociation from this complex has been evaluated under in vitro and in vivo conditions and is extremely slow. Dutasteride does not bind to the human androgen receptor.

Tamsulosin

Smooth muscle tone is mediated by the sympathetic nervous stimulation of alpha1-adrenoceptors, which are abundant in the prostate, prostatic capsule, prostatic urethra, and bladder neck. Blockade of these adrenoceptors can cause smooth muscles in the bladder neck and prostate to relax, resulting in an improvement in urine flow rate and a reduction in symptoms of BPH.

Tamsulosin, an alpha1-adrenoceptor blocking agent, exhibits selectivity for alpha1-receptors in the human prostate. At least 3 discrete alpha1-adrenoceptor subtypes have been identified: alpha1A, alpha1B, and alpha1D; their distribution differs between human organs and tissue. Approximately 70% of the alpha1-receptors in human prostate are of the alpha1A subtype. Tamsulosin is not intended for use as an antihypertensive.

12.2 Pharmacodynamics

Dutasteride

Effect on 5 Alpha-Dihydrotestosterone and Testosterone: The maximum effect of daily doses of dutasteride on the reduction of DHT is dose-dependent and is observed within 1 to 2 weeks. After 1 and 2 weeks of daily dosing with dutasteride 0.5 mg, median serum DHT concentrations were reduced by 85% and 90%, respectively. In patients with BPH treated with dutasteride 0.5 mg/day for 4 years, the median decrease in serum DHT was 94% at 1 year, 93% at 2 years, and 95% at both 3 and 4 years. The median increase in serum testosterone was 19% at both 1 and 2 years, 26% at 3 years, and 22% at 4 years, but the mean and median levels remained within the physiologic range.

In patients with BPH treated with 5 mg/day of dutasteride or placebo for up to 12 weeks prior to transurethral resection of the prostate, mean DHT concentrations in prostatic tissue were significantly lower in the dutasteride group compared with placebo (784 and 5,793 pg/g, respectively, P<0.001). Mean prostatic tissue concentrations of testosterone were significantly higher in the dutasteride group compared with placebo (2,073 and 93 pg/g, respectively, P<0.001).

Adult males with genetically inherited type 2 5-alpha-reductase deficiency also have decreased DHT levels. These 5-alpha-reductase-deficient males have a small prostate gland throughout life and do not develop BPH. Except for the associated urogenital defects present at birth, no other clinical abnormalities related to 5-alpha-reductase deficiency have been observed in these individuals.

Effects on Other Hormones: In healthy volunteers, 52 weeks of treatment with dutasteride 0.5 mg/day (n = 26) resulted in no clinically significant change compared with placebo (n = 23) in sex hormone-binding globulin, estradiol, luteinizing hormone, follicle-stimulating hormone, thyroxine (free T4), and dehydroepiandrosterone. Statistically significant, baseline-adjusted mean increases compared with placebo were observed for total testosterone at 8 weeks (97.1 ng/dL, P<0.003) and thyroid-stimulating hormone at 52 weeks (0.4 mcIU/mL, P<0.05). The median percentage changes from baseline within the dutasteride group were 17.9% for testosterone at 8 weeks and 12.4% for thyroid-stimulating hormone at 52 weeks. After stopping dutasteride for 24 weeks, the mean levels of testosterone and thyroid-stimulating hormone had returned to baseline in the group of subjects with available data at the visit. In subjects with BPH treated with dutasteride in a large randomized, double-blind, placebo-controlled trial, there was a median percent increase in luteinizing hormone of 12% at 6 months and 19% at both 12 and 24 months.

Other Effects: Plasma lipid panel and bone mineral density were evaluated following 52 weeks of dutasteride 0.5 mg once daily in healthy volunteers. There was no change in bone mineral density as measured by dual energy x-ray absorptiometry compared with either placebo or baseline. In addition, the plasma lipid profile (i.e., total cholesterol, low density lipoproteins, high density lipoproteins, triglycerides) was unaffected by dutasteride. No clinically significant changes in adrenal hormone responses to adrenocorticotropic hormone (ACTH) stimulation were observed in a subset population (n = 13) of the 1-year healthy volunteer trial.

12.3 Pharmacokinetics

The pharmacokinetics of dutasteride and tamsulosin from JALYN are comparable to the pharmacokinetics of dutasteride and tamsulosin when administered separately.

Absorption

The pharmacokinetic parameters of dutasteride and tamsulosin observed after administration of JALYN in a single-dose, randomized, 3-period, partial cross-over trial are summarized in Table 2 below.

Table 2. Arithmetic Means (SD) of Serum Dutasteride and Tamsulosin in Single-dose Pharmacokinetic Parameters under Fed Conditions
Component | N | AUC(0-t) (ng h/mL) | Cmax (ng/mL) | Tmax (h) [Median (range).] | t½ (h)
Dutasteride | 92 | 39.6 (23.1) | 2.14 (0.77) | 3.00 (1.00-10.00)
Tamsulosin | 92 | 187.2 (95.7) | 11.3 (4.44) | 6.00 (2.00-24.00) | 13.5 (3.92) [N = 91.]

Dutasteride: Following administration of a single 0.5-mg dose of a soft gelatin capsule, time to peak absolute bioavailability in 5 healthy subjects is approximately 60% (range: 40% to 94%).

Tamsulosin: Absorption of tamsulosin is essentially complete (>90%) following oral administration of 0.4-mg tamsulosin hydrochloride capsules under fasting conditions. Tamsulosin exhibits linear kinetics following single and multiple dosing, with achievement of steady-state concentrations by the fifth day of once-daily dosing.

Effect of Food

Food does not affect the pharmacokinetics of dutasteride following administration of JALYN. However, a mean 30% decrease in tamsulosin Cmax was observed when JALYN was administered with food, similar to that seen when tamsulosin monotherapy was administered under fed versus fasting conditions.

Distribution

Dutasteride: Pharmacokinetic data following single and repeat oral doses show that dutasteride has a large volume of distribution (300 to 500 L). Dutasteride is highly bound to plasma albumin (99.0%) and alpha-1 acid glycoprotein (AAG, 96.6%).

In a trial of healthy subjects (n = 26) receiving dutasteride 0.5 mg/day for 12 months, semen dutasteride concentrations averaged 3.4 ng/mL (range: 0.4 to 14 ng/mL) at 12 months and, similar to serum, achieved steady-state concentrations at 6 months. On average, at 12 months 11.5% of serum dutasteride concentrations partitioned into semen.

Tamsulosin: The mean steady-state apparent volume of distribution of tamsulosin after intravenous administration to 10 healthy male adults was 16 L, which is suggestive of distribution into extracellular fluids in the body.

Tamsulosin is extensively bound to human plasma proteins (94% to 99%), primarily AAG, with linear binding over a wide concentration range (20 to 600 ng/mL).

The results of 2-way in vitro studies indicate that the binding of tamsulosin to human plasma proteins is not affected by amitriptyline, diclofenac, glyburide, simvastatin plus simvastatin-hydroxy acid metabolite, warfarin, diazepam, or propranolol.

Likewise, tamsulosin had no effect on the extent of binding of these drugs.

Metabolism

Dutasteride: Dutasteride is extensively metabolized in humans. In vitro studies showed that dutasteride is metabolized by the CYP3A4 and CYP3A5 isoenzymes. Both of these isoenzymes produced the 4'-hydroxydutasteride, 6-hydroxydutasteride, and the 6,4'-dihydroxydutasteride metabolites. In addition, the 15-hydroxydutasteride metabolite was formed by CYP3A4. Dutasteride is not metabolized in vitro by human cytochrome P450 isoenzymes CYP1A2, CYP2A6, CYP2B6, CYP2C8, CYP2C9, CYP2C19, CYP2D6, and CYP2E1. In human serum following dosing to steady state, unchanged dutasteride, 3 major metabolites (4'-hydroxydutasteride, 1,2-dihydrodutasteride, and 6-hydroxydutasteride), and 2 minor metabolites (6,4'-dihydroxydutasteride and 15-hydroxydutasteride), as assessed by mass spectrometric response, have been detected. The absolute stereochemistry of the hydroxyl additions in the 6 and 15 positions is not known. In vitro, the 4'-hydroxydutasteride and 1,2-dihydrodutasteride metabolites are much less potent than dutasteride against both isoforms of human 5α-reductase. The activity of 6β-hydroxydutasteride is comparable to that of dutasteride.

Tamsulosin: There is no enantiomeric bioconversion from tamsulosin [R(-) isomer] to the S(+) isomer in humans. Tamsulosin is extensively metabolized by cytochrome P450 enzymes in the liver and less than 10% of the dose is excreted in urine unchanged. However, the pharmacokinetic profile of the metabolites in humans has not been established. In vitro studies indicate that CYP3A4 and CYP2D6 are involved in metabolism of tamsulosin as well as some minor participation of other CYP isoenzymes. Inhibition of hepatic drug-metabolizing enzymes may lead to increased exposure to tamsulosin [see Drug Interactions (7.1)]. The metabolites of tamsulosin undergo extensive conjugation to glucuronide or sulfate prior to renal excretion.

Incubations with human liver microsomes showed no evidence of clinically significant metabolic interactions between tamsulosin and amitriptyline, albuterol, glyburide, and finasteride. However, results of the in vitro testing of the tamsulosin interaction with diclofenac and warfarin were equivocal.

Excretion

Dutasteride: Dutasteride and its metabolites were excreted mainly in feces. As a percent of dose, there was approximately 5% unchanged dutasteride (approximately 1% to approximately 15%) and 40% as dutasteride-related metabolites (approximately 2% to approximately 90%). Only trace amounts of unchanged dutasteride were found in urine (<1%). Therefore, on average, the dose unaccounted for approximated 55% (range: 5% to 97%). The terminal elimination half-life of dutasteride is approximately 5 weeks at steady state. The average steady-state serum dutasteride concentration was 40 ng/mL following 0.5 mg/day for 1 year. Following daily dosing, dutasteride serum concentrations achieve 65% of steady-state concentration after 1 month and approximately 90% after 3 months. Due to the long half-life of dutasteride, serum concentrations remain detectable (greater than 0.1 ng/mL) for up to 4 to 6 months after discontinuation of treatment.

Tamsulosin: On administration of the radiolabeled dose of tamsulosin to 4 healthy volunteers, 97% of the administered radioactivity was recovered, with urine (76%) representing the primary route of excretion compared with feces (21%) over 168 hours.

Following intravenous or oral administration of an immediate-release formulation, the elimination half-life of tamsulosin in plasma ranges from 5 to 7 hours.

Because of absorption rate-controlled pharmacokinetics with tamsulosin hydrochloride capsules, the apparent half-life of tamsulosin is approximately 9 to 13 hours in healthy volunteers and 14 to 15 hours in the target population.

Tamsulosin undergoes restrictive clearance in humans, with a relatively low systemic clearance (2.88 L/h).

Specific Populations

Pediatric Patients: The pharmacokinetics of dutasteride and tamsulosin administered together have not been investigated in subjects younger than 18 years.

Geriatric Patients: Dutasteride and tamsulosin pharmacokinetics using JALYN have not been studied in geriatric patients. The following text reflects information for the individual components.

Dutasteride: No dosage adjustment is necessary in the elderly.

The pharmacokinetics and pharmacodynamics of dutasteride were evaluated in 36 healthy male subjects aged between 24 and 87 years following administration of a single 5-mg dose of dutasteride. In this single-dose trial, dutasteride half-life increased with age (approximately 170 hours in men aged 20 to 49 years, approximately 260 hours in men aged 50 to 69 years, and approximately 300 hours in men older than 70 years).

Tamsulosin: Cross-study comparison of tamsulosin overall exposure (AUC) and half-life indicate that the pharmacokinetic disposition of tamsulosin may be slightly prolonged in geriatric males compared with young, healthy male volunteers. Intrinsic clearance is independent of tamsulosin binding to AAG, but diminishes with age, resulting in a 40% overall higher exposure (AUC) in subjects aged 55 to 75 years compared with subjects aged 20 to 32 years.

Male and Female Patients: Dutasteride: Dutasteride is contraindicated in females who are pregnant and is not indicated for use in females [see Contraindications (4), Warnings and Precautions (5.6)]. The pharmacokinetics of dutasteride in females have not been studied.

Tamsulosin: Tamsulosin is not indicated for use in females. No information is available on the pharmacokinetics of tamsulosin in females.

Racial and Ethnic Groups: The effect of race on the pharmacokinetics of dutasteride and tamsulosin administered together or separately has not been studied.

Patients with Renal Impairment: The effect of renal impairment on dutasteride and tamsulosin pharmacokinetics has not been studied using JALYN. The following text reflects information for the individual components.

Dutasteride: The effect of renal impairment on dutasteride pharmacokinetics has not been studied. However, less than 0.1% of a steady-state 0.5-mg dose of dutasteride is recovered in human urine, so no adjustment in dosage is anticipated for patients with renal impairment.

Tamsulosin: The pharmacokinetics of tamsulosin have been compared in 6 subjects with mild-moderate (30≤ CLcr <70 mL/min/1.73 m^2) or moderate-severe (10≤ CLcr <30 mL/min/1.73 m^2) renal impairment and 6 normal subjects (CLcr >90 mL/min/1.73 m^2). While a change in the overall plasma concentration of tamsulosin was observed as the result of altered binding to AAG, the unbound (active) concentration of tamsulosin, as well as the intrinsic clearance, remained relatively constant. Therefore, patients with renal impairment do not require an adjustment in tamsulosin dosing. However, patients with end-stage renal disease (CLcr <10 mL/min/1.73 m^2) have not been studied.

Patients with Hepatic Impairment: The effect of hepatic impairment on dutasteride and tamsulosin pharmacokinetics has not been studied using JALYN. The following text reflects information available for the individual components.

Dutasteride: The effect of hepatic impairment on dutasteride pharmacokinetics has not been studied. Because dutasteride is extensively metabolized, exposure could be higher in hepatically impaired patients.

Tamsulosin: The pharmacokinetics of tamsulosin have been compared in 8 subjects with moderate hepatic impairment (Child-Pugh classification: Grades A and B) and 8 normal subjects. While a change in the overall plasma concentration of tamsulosin was observed as the result of altered binding to AAG, the unbound (active) concentration of tamsulosin does not change significantly with only a modest (32%) change in intrinsic clearance of unbound tamsulosin. Therefore, patients with moderate hepatic impairment do not require an adjustment in tamsulosin dosage. Tamsulosin has not been studied in patients with severe hepatic impairment.

Drug Interaction Studies

There have been no drug interaction studies using JALYN. The following text reflects information available for the individual components.

Cytochrome P450 Inhibitors: Dutasteride: No clinical drug interaction trials have been performed to evaluate the impact of CYP3A enzyme inhibitors on dutasteride pharmacokinetics. However, based on in vitro data, blood concentrations of dutasteride may increase in the presence of inhibitors of CYP3A4/5 such as ritonavir, ketoconazole, verapamil, diltiazem, cimetidine, troleandomycin, and ciprofloxacin.

Dutasteride does not inhibit the in vitro metabolism of model substrates for the major human cytochrome P450 isoenzymes (CYP1A2, CYP2C9, CYP2C19, CYP2D6, and CYP3A4) at a concentration of 1,000 ng/mL, 25 times greater than steady-state serum concentrations in humans.

Tamsulosin: Strong and Moderate Inhibitors of CYP3A4 or CYP2D6: The effects of ketoconazole (a strong inhibitor of CYP3A4) at 400 mg once daily for 5 days on the pharmacokinetics of a single tamsulosin hydrochloride capsule 0.4-mg dose was investigated in 24 healthy volunteers (age range: 23 to 47 years). Concomitant treatment with ketoconazole resulted in increases in the Cmax and AUC of tamsulosin by factors of 2.2 and 2.8, respectively. The effects of concomitant administration of a moderate CYP3A4 inhibitor (e.g., erythromycin) on the pharmacokinetics of tamsulosin have not been evaluated.

The effects of paroxetine (a strong inhibitor of CYP2D6) at 20 mg once daily for 9 days on the pharmacokinetics of a single tamsulosin capsule 0.4-mg dose was investigated in 24 healthy volunteers (age range: 23 to 47 years). Concomitant treatment with paroxetine resulted in increases in the Cmax and AUC of tamsulosin by factors of 1.3 and 1.6, respectively. A similar increase in exposure is expected in poor metabolizers (PM) of CYP2D6 as compared with extensive metabolizers (EM). A fraction of the population (about 7% of whites and 2% of African-Americans) are CYP2D6 PMs. Since CYP2D6 PMs cannot be readily identified and the potential for significant increase in tamsulosin exposure exists when tamsulosin 0.4 mg is coadministered with strong CYP3A4 inhibitors in CYP2D6 PMs, tamsulosin 0.4-mg capsules should not be used in combination with strong inhibitors of CYP3A4 (e.g., ketoconazole).

The effects of concomitant administration of a moderate CYP2D6 inhibitor (e.g., terbinafine) on the pharmacokinetics of tamsulosin have not been evaluated.

The effects of coadministration of both a CYP3A4 and a CYP2D6 inhibitor with tamsulosin capsules have not been evaluated. However, there is a potential for significant increase in tamsulosin exposure when tamsulosin 0.4 mg is coadministered with a combination of both CYP3A4 and CYP2D6 inhibitors.

Cimetidine: The effects of cimetidine at the highest recommended dose (400 mg every 6 hours for 6 days) on the pharmacokinetics of a single tamsulosin capsule 0.4-mg dose was investigated in 10 healthy volunteers (age range: 21 to 38 years). Treatment with cimetidine resulted in a significant decrease (26%) in the clearance of tamsulosin hydrochloride, which resulted in a moderate increase in tamsulosin hydrochloride AUC (44%).

Alpha-adrenergic Antagonists: Dutasteride: In a single-sequence, crossover trial in healthy volunteers, the administration of tamsulosin or terazosin in combination with dutasteride had no effect on the steady-state pharmacokinetics of either alpha-adrenergic antagonist. Although the effect of administration of tamsulosin or terazosin on dutasteride pharmacokinetic parameters was not evaluated, the percent change in DHT concentrations was similar for dutasteride, alone or in combination with tamsulosin or terazosin.

Warfarin: Dutasteride: In a trial of 23 healthy volunteers, 3 weeks of treatment with dutasteride 0.5 mg/day did not alter the steady-state pharmacokinetics of the S- or R-warfarin isomers or alter the effect of warfarin on prothrombin time when administered with warfarin.

Tamsulosin: A definitive drug-drug interaction trial between tamsulosin and warfarin was not conducted. Results from limited in vitro and in vivo studies are inconclusive. Therefore, caution should be exercised with concomitant administration of warfarin and tamsulosin.

Nifedipine, Atenolol, Enalapril: Tamsulosin: In 3 trials in hypertensive subjects (age range: 47 to 79 years) whose blood pressure was controlled with stable doses of nifedipine extended-release, atenolol, or enalapril for at least 3 months, tamsulosin hydrochloride capsules 0.4 mg for 7 days followed by tamsulosin hydrochloride capsules 0.8 mg for another 7 days (n = 8 per trial) resulted in no clinically significant effects on blood pressure and pulse rate compared with placebo (n = 4 per trial). Therefore, dosage adjustments are not necessary when tamsulosin is administered concomitantly with nifedipine extended-release, atenolol, or enalapril.

Digoxin and Theophylline: Dutasteride: In a trial of 20 healthy volunteers, dutasteride did not alter the steady-state pharmacokinetics of digoxin when administered concomitantly at a dose of 0.5 mg/day for 3 weeks.

Tamsulosin: In 2 trials in healthy volunteers (n=10 per trial, age range: 19 to 39 years) receiving tamsulosin capsules 0.4 mg/day for 2 days, followed by tamsulosin capsules 0.8 mg/day for 5 to 8 days, single intravenous doses of digoxin 0.5 mg or theophylline 5 mg/kg resulted in no change in the pharmacokinetics of digoxin or theophylline. Therefore, dosage adjustments are not necessary when a tamsulosin capsule is administered concomitantly with digoxin or theophylline.

Furosemide: Tamsulosin: The pharmacokinetic and pharmacodynamic interaction between tamsulosin hydrochloride capsules 0.8 mg/day (steady-state) and furosemide 20 mg intravenously (single dose) was evaluated in 10 healthy volunteers (age range: 21 to 40 years). Tamsulosin had no effect on the pharmacodynamics (excretion of electrolytes) of furosemide. While furosemide produced an 11% to 12% reduction in tamsulosin Cmax and AUC, these changes are expected to be clinically insignificant and do not require dose adjustment for tamsulosin.

Calcium Channel Antagonists: Dutasteride: In a population pharmacokinetics analysis, a decrease in clearance of dutasteride was noted when coadministered with the CYP3A4 inhibitors verapamil (-37%, n = 6) and diltiazem (-44%, n = 5). In contrast, no decrease in clearance was seen when amlodipine, another calcium channel antagonist that is not a CYP3A4 inhibitor, was coadministered with dutasteride (+7%, n = 4). The decrease in clearance and subsequent increase in exposure to dutasteride in the presence of verapamil and diltiazem is not considered to be clinically significant. No dosage adjustment is recommended.

Cholestyramine: Dutasteride: Administration of a single 5-mg dose of dutasteride followed 1 hour later by 12 g cholestyramine did not affect the relative bioavailability of dutasteride in 12 normal volunteers.

13 NONCLINICAL TOXICOLOGY

13.1 Carcinogenesis, Mutagenesis, Impairment of Fertility

No non-clinical studies have been conducted with JALYN. The following information is based on studies performed with dutasteride or tamsulosin.

Carcinogenesis

Dutasteride: A 2-year carcinogenicity study was conducted in B6C3F1 mice at doses of 3, 35, 250, and 500 mg/kg/day for males and 3, 35, and 250 mg/kg/day for females; an increased incidence of benign hepatocellular adenomas was noted at 250 mg/kg/day (290-fold the MRHD of a 0.5-mg daily dose) in female mice only. Two of the 3 major human metabolites have been detected in mice. The exposure to these metabolites in mice is either lower than in humans or is not known.

In a 2-year carcinogenicity study in Han Wistar rats, at doses of 1.5, 7.5, and 53 mg/kg/day in males and 0.8, 6.3, and 15 mg/kg/day in females, there was an increase in Leydig cell adenomas in the testes at 135-fold the MRHD (53 mg/kg/day and greater). An increased incidence of Leydig cell hyperplasia was present at 52-fold the MRHD (male rat doses of 7.5 mg/kg/day and greater). A positive correlation between proliferative changes in the Leydig cells and an increase in circulating luteinizing hormone levels has been demonstrated with 5-alpha-reductase inhibitors and is consistent with an effect on the hypothalamic-pituitary-testicular axis following 5-alpha-reductase inhibition. At tumorigenic doses, luteinizing hormone levels in rats were increased by 167%. In this study, the major human metabolites were tested for carcinogenicity at approximately 1 to 3 times the expected clinical exposure.

Tamsulosin: In a rat carcinogenicity assay, no increases in tumor incidence was observed in rats administered up to 3 times the MRHD of 0.8 mg/day (based on AUC of animal doses up to 43 mg/kg/day in males and up to 52 mg/kg/day in females), with the exception of a modest increase in the frequency of mammary gland fibroadenomas in female rats receiving doses of 5.4 mg/kg or greater.

In a carcinogenicity assay, mice were administered up to 8 times the MRHD of tamsulosin (oral doses up to 127 mg/kg/day in males and 158 mg/kg/day in females). There were no significant tumor findings in male mice. Female mice treated for 2 years with the 2 highest doses of 45 and 158 mg/kg/day had statistically significant increases in the incidence of mammary gland fibroadenomas (P<0.0001) and adenocarcinomas.

The increased incidences of mammary gland neoplasms in female rats and mice were considered secondary to tamsulosin-induced hyperprolactinemia. It is not known if tamsulosin elevates prolactin in humans. The relevance for human risk of the findings of prolactin-mediated endocrine tumors in rodents is not known.

Mutagenesis

Dutasteride: Dutasteride was tested for genotoxicity in a bacterial mutagenesis assay (Ames test), a chromosomal aberration assay in Chinese hamster ovary (CHO) cells, and a micronucleus assay in rats. The results did not indicate any genotoxic potential of the parent drug. Two major human metabolites were also negative in either the Ames test or an abbreviated Ames test.

Tamsulosin: Tamsulosin produced no evidence of mutagenic potential in vitro in the Ames reverse mutation test, mouse lymphoma thymidine kinase assay, unscheduled DNA repair synthesis assay, and chromosomal aberration assays in CHO cells or human lymphocytes. There were no mutagenic effects in the in vivo sister chromatid exchange and mouse micronucleus assay.

Impairment of Fertility

Dutasteride: Treatment of sexually mature male rats with dutasteride at 0.1 times the MRHD (animal doses of 0.05 mg/kg/day or greater for up to 31 weeks) based on mean serum concentration resulted in dose- and time-dependent decreases in fertility at all doses; reduced cauda epididymal (absolute) sperm counts but not sperm concentration (at 50 and 500 mg/kg/day); reduced weights of the epididymis, prostate, and seminal vesicles; and microscopic changes (cytoplasmic vacuolation of tubular epithelium in the epididymides and/or decreased cytoplasmic content of epithelium, consistent with decreased secretory activity in the prostate and seminal vesicles) in the reproductive organs at all doses in the absence of paternal toxicity. The fertility effects were reversed by Recovery Week 6 at all doses, and sperm counts were normal at the end of a 14-week recovery period. The microscopic changes were no longer present at Recovery Week 14 at 0.1 times the MRHD and were partly recovered in the remaining treatment groups. Low levels of dutasteride (0.6 to 17 ng/mL) were detected in the serum of untreated female rats mated to treated males (10 to 500 mg/kg/day for 29 to 30 weeks) which are 16 to 110 times the MRHD based on mean serum concentration. No feminization occurred in male offspring of untreated female rats mated to treated male rats even though detectable blood levels of dutasteride were observed in the female rats.

In a fertility study in female rats with dosing 4 weeks prior to mating through early gestation, oral administration of dutasteride at doses of 0.05, 2.5, 12.5, and 30 mg/kg/day resulted in reduced litter size due to increased resorptions and in feminization of male fetuses (decreased anogenital distance) at 2 to 10 times the MRHD (animal doses of 2.5 mg/kg/day or greater) based on mean serum concentration, in the presence of maternal toxicity (decreased body weight gain). Fetal body weights were also reduced at approximately 0.02 times the MRHD (rat dose of 0.05 mg/kg/day or greater) based on mean serum concentration, with no no-effect level, in the absence of maternal toxicity.

Tamsulosin: Studies in rats revealed significantly reduced fertility in males dosed with single or multiple daily doses of 300 mg/kg/day of tamsulosin hydrochloride (AUC exposure in rats about 50 times the human exposure with the maximum therapeutic dose). The mechanism of decreased fertility in male rats is considered to be an effect of the compound on the vaginal plug formation possibly due to changes of semen content or impairment of ejaculation. The effects on fertility were reversible, showing improvement by 3 days after a single dose and 4 weeks after multiple daily dosing. Effects on fertility in males were completely reversed within 9 weeks after discontinuation of multiple daily dosing. Multiple doses of 10 and 100 mg/kg/day tamsulosin hydrochloride (1/5 and 16 times the anticipated human AUC exposure) did not significantly alter fertility in male rats. Effects of tamsulosin on sperm counts or sperm function have not been evaluated.

Studies in female rats revealed significant reductions in fertility after single or multiple daily doses of 300 mg/kg/day of the R-isomer or racemic mixture of tamsulosin hydrochloride, respectively. In female rats, the reductions in fertility after single doses were considered to be associated with impairments in fertilization. Multiple daily doses of 10 or 100 mg/kg/day of the racemic mixture did not significantly alter fertility in female rats.

13.2 Animal Toxicology and/or Pharmacology

Central Nervous System Toxicology Studies

Dutasteride: In rats and dogs, repeated oral administration of dutasteride resulted in some animals showing signs of non-specific, reversible, centrally-mediated toxicity without associated histopathological changes at exposures 425- and 315-fold the expected clinical exposure (of parent drug), respectively.

Rabbit Dermal Absorption

In a rabbit dermal pharmacokinetics study, dermal absorption of dutasteride in CAPMUL (glyceryl oleate) in rabbits resulted in serum concentrations of 2.7 to 40.5 mcg/h/mL for doses of 1 to 20 mg/mL, respectively, or 56% to 100% of applied dutasteride to be absorbed under occluded and prolonged conditions. JALYN soft gelatin capsules administered orally contain 0.5 mg dutasteride dissolved in a mixture of mono-di-glycerides of caprylic/capric acid and butylated hydroxytoluene. Dutasteride in water was minimally absorbed in rabbits (2,000 mg/kg).

14 CLINICAL STUDIES

The trial supporting the efficacy of JALYN was a 4-year multicenter, randomized, double-blind, parallel-group trial (CombAT trial) investigating the efficacy of the coadministration of dutasteride 0.5 mg/day and tamsulosin hydrochloride 0.4 mg/day (n = 1,610) compared with dutasteride alone (n = 1,623) or tamsulosin alone (n = 1,611). Subjects were aged at least 50 years with a serum PSA ≥1.5 ng/mL and <10 ng/mL and BPH diagnosed by medical history and physical examination, including enlarged prostate (≥30 cc) and BPH symptoms that were moderate to severe according to the International Prostate Symptom Score (IPSS). Eighty-eight percent (88%) of the enrolled trial population was white. Approximately 52% of subjects had previous exposure to 5-alpha-reductase inhibitor or alpha-adrenergic antagonist treatment. Of the 4,844 subjects randomly assigned to receive treatment, 69% of subjects in the coadministration group, 67% in the dutasteride group, and 61% in the tamsulosin group completed 4 years of double-blind treatment.

Effect on Symptom Score

Symptoms were quantified using the first 7 questions of the International Prostate Symptom Score (IPSS). The baseline score was approximately 16.4 units for each treatment group. Coadministration therapy was statistically superior to each of the monotherapy treatments in decreasing symptom score at Month 24, the primary time point for this endpoint. At Month 24, the mean changes from baseline (±SD) in IPSS total symptom scores were -6.2 (±7.14) for the coadministration group, -4.9 (±6.81) for dutasteride, and -4.3 (±7.01) for tamsulosin, with a mean difference between coadministration and dutasteride of -1.3 units (P<0.001; [95% CI: -1.69, -0.86]), and between coadministration and tamsulosin of -1.8 units (P<0.001; [95% CI: -2.23, -1.40]). A significant difference was seen by Month 9 and continued through Month 48.

At Month 48 the mean changes from baseline (±SD) in IPSS total symptom scores were -6.3 (±7.40) for coadministration, -5.3 (±7.14) for dutasteride, and -3.8 (±7.74) for tamsulosin, with a mean difference between coadministration and dutasteride of -0.96 units (P<0.001; [95% CI: -1.40, -0.52]), and between coadministration and tamsulosin of -2.5 units (P<0.001; [95% CI: -2.96, -2.07]). See Figure 1.

Figure 1. International Prostate Symptom Score Change from Baseline over a 48-Month Period (Randomized, Double-blind, Parallel-group Trial [CombAT Trial])

Effect on Acute Urinary Retention (AUR) or the Need for BPH-related Surgery

After 4 years of treatment, coadministration therapy with dutasteride and tamsulosin did not provide benefit over dutasteride monotherapy in reducing the incidence of AUR or BPH-related surgery.

In separate 2-year randomized, double-blind trials, compared with placebo, dutasteride monotherapy was associated with a statistically significantly lower incidence of AUR (1.8% for dutasteride versus 4.2% for placebo; 57% reduction in risk) and with a statistically significantly lower incidence of BPH-related surgery (2.2% for dutasteride versus. 4.1% for placebo; 48% reduction in risk).

Effect on Maximum Urine Flow Rate

The baseline Qmax was approximately 10.7 mL/sec for each treatment group. Coadministration therapy was statistically superior to each of the monotherapy treatments in increasing Qmax at Month 24, the primary time point for this endpoınt. At Month 24, the mean increases from baseline (±SD) in Qmax were 2.4 (±5.26) mL/sec for coadministration group, 1.9 (±5.10) mL/sec for dutasteride, and 0.9 (±4.57) mL/sec for tamsulosin, with a mean difference between coadministration and dutasteride of 0.5 mL/sec (P = 0.003; [95% CI: 0.17, 0.84]), and between coadministration and tamsulosin of 1.5 mL/sec (P<0.001; [95% CI: 1.19, 1.86]). This difference was seen by Month 6 and continued through Month 24. See Figure 2.

The additional improvement in Qmax of coadministration therapy over dutasteride monotherapy was no longer statistically significant at Month 48.

Figure 2. Qmax Change from Baseline over a 24-Month Period (Randomized, Double-blind, Parallel-group Trial [CombAT Trial])

Effect on Prostate Volume

The mean prostate volume at trial entry was approximately 55 cc. At Month 24, the primary time point for this endpoint, the mean percent changes from baseline (±SD) in prostate volume were -26.9% (±22.57) for coadministration therapy, -28.0% (±24.88) for dutasteride, and 0% (±31.14) for tamsulosin, with a mean difference between coadministration and dutasteride of 1.1% (P = NS; [95% CI: -0.6, 2.8]), and between coadministration and tamsulosin of -26.9% (P<0.001; [95% CI: -28.9, -24.9]). Similar changes were seen at Month 48: -27.3% (±24.91) for coadministration therapy, -28.0% (±25.74) for dutasteride, and +4.6% (±35.45) for tamsulosin.

16 HOW SUPPLIED/STORAGE AND HANDLING

JALYN capsules, containing 0.5 mg dutasteride and 0.4 mg tamsulosin hydrochloride, are oblong hard-shell capsules with a brown body and an orange cap imprinted with "GS 7CZ" in black ink. They are available in bottles with child-resistant closures as follows:

Bottle of 30 | (NDC 80725-809-13).
Bottle of 90 | (NDC 80725-809-59).

STORAGE AND HANDLING

Store at 25°C (77°F); excursions permitted 15° to 30°C (59° to 86°F) [see USP Controlled Room Temperature]. Capsules may become deformed and/or discolored if kept at high temperatures.

Dutasteride is absorbed through the skin. JALYN capsules should not be handled by females who are pregnant or who could become pregnant because of the potential for absorption of dutasteride and the subsequent potential risk to a developing male fetus [see Warnings and Precautions (5.6)].

17 PATIENT COUNSELING INFORMATION

Advise the patient to read the FDA-approved patient labeling (Patient Information).

Orthostatic Hypotension

Inform patients about the possible occurrence of symptoms related to orthostatic hypotension, such as dizziness and vertigo, and the potential risk of syncope when taking JALYN. Caution patients starting treatment with JALYN to avoid situations where injury could result should syncope occur (e.g., driving, operating machinery, performing hazardous tasks). Advise patients to sit or lie down at the first signs of orthostatic hypotension [see Warnings and Precautions (5.1)].

Drug Interactions

Advise patients that JALYN should not be used in combination with strong inhibitors of CYP3A4 [see Warnings and Precautions (5.2), Drug Interactions (7.1)].

PSA Monitoring

Inform patients that JALYN reduces serum PSA levels by approximately 50% within 3 to 6 months of therapy, although it may vary for each individual. For patients undergoing PSA screening, increases in PSA levels while on treatment with JALYN may signal the presence of prostate cancer and should be evaluated by a healthcare provider [see Warnings and Precautions (5.3)].

Increased Risk of High-Grade Prostate Cancer

Inform patients that there was an increase in high-grade prostate cancer in men treated with 5-alpha-reductase inhibitors (which are indicated for BPH treatment), including dutasteride, which is a component of JALYN, compared with those treated with placebo in trials looking at the use of these drugs to reduce the risk of prostate cancer [see Indications and Usage (1.2), Warnings and Precautions (5.4), Adverse Reactions (6.1)].

Transdermal Exposure of JALYN in Pregnant or Potentially Pregnant Females—Risk to Male Fetus

Inform patients that JALYN capsules should not be handled by females who are pregnant or may potentially be pregnant because of the potential for absorption of dutasteride and the subsequent potential risk to a developing male fetus. Dutasteride can be absorbed through the skin and could result in unintended fetal exposure. If a pregnant or potentially pregnant female comes in contact with leaking JALYN capsules, the contact area should be washed immediately with soap and water [see Warnings and Precautions (5.6), Use in Specific Populations (8.1)].

Effects on Semen Parameters

Advise men that JALYN may affect sperm characteristics but the effect on fertility is unknown [see Warnings and Precautions (5.11), Use in Specific Populations (8.3)].

Administration Instructions

JALYN capsules should be swallowed whole and not chewed, crushed, or opened. JALYN capsules may become deformed and/or discolored if kept at high temperatures. If this occurs, capsules should not be used.

Priapism

Inform patients about the possibility of priapism as a result of treatment with JALYN or other alpha-adrenergic–antagonist-containing medications. Inform patients that this reaction is extremely rare, but can lead to permanent erectile dysfunction if not brought to immediate medical attention [see Warnings and Precautions (5.7)].

Blood Donation

Inform men treated with JALYN that they should not donate blood until at least 6 months following their last dose to prevent pregnant females from receiving dutasteride through blood transfusion [see Warnings and Precautions (5.8)]. Serum levels of dutasteride are detectable for 4 to 6 months after treatment ends [see Clinical Pharmacology (12.3)].

Intraoperative Floppy Iris Syndrome (IFIS)

Advise patients considering cataract or glaucoma surgery to tell their ophthalmologist that they take or have taken JALYN, an alpha-adrenergic–antagonist-containing product [see Warnings and Precautions (5.9)].

The other brands listed are trademarks owned by or licensed to their respective owners and are not owned by or licensed to Waylis Therepeutics LLC. The makers of these brands are not affiliated with and does not endorse Waylis Therepeutics LLC or its products.

Manufactured for:
Waylis Therapeutics LLC
Rahway, NJ 07065

PATIENT INFORMATION JALYN (JAY-lin) (dutasteride and tamsulosin hydrochloride) capsules

JALYN is for use by men only.

What is JALYN?

JALYN is a prescription medicine that contains 2 medicines: dutasteride and tamsulosin. JALYN is used to treat the symptoms of benign prostatic hyperplasia (BPH) in men with an enlarged prostate. The 2 medications in JALYN work in different ways to improve symptoms of BPH. Dutasteride shrinks the enlarged prostate and tamsulosin relaxes muscles in the prostate and neck of the bladder. These 2 medications, when used together, can improve symptoms of BPH better than either medication when used alone.

Do not take JALYN if you are:

- pregnant or may be pregnant. JALYN may harm your unborn baby. Pregnant females should not touch JALYN capsules. If a female who is pregnant with a male baby gets enough JALYN in her body by swallowing or touching JALYN, the male baby may be born with sex organs that are not normal. If a pregnant female comes in contact with leaking JALYN capsules, the contact area should be washed immediately with soap and water.
- allergic to dutasteride, tamsulosin, or any of the ingredients in JALYN.

See the end of this leaflet for a complete list of ingredients in JALYN.

- taking another medicine that contains an alpha-blocker.
- allergic to other 5-alpha-reductase inhibitors, for example, PROSCAR (finasteride) tablets.

Before you take JALYN, tell your healthcare provider about all of your medical conditions, including if you:

- have a history of low blood pressure
- take medicines to treat high blood pressure
- plan to have cataract or glaucoma surgery
- have liver problems
- are allergic to sulfa medications
- have any other medical conditions

Tell your healthcare provider about all the medicines you take, including prescription and over-the-counter medicines, vitamins, and herbal supplements. JALYN and other medicines may affect each other, causing side effects. JALYN may affect the way other medicines work, and other medicines may affect how JALYN works.

Know the medicines you take. Keep a list of them to show your healthcare provider and pharmacist when you get a new medicine.

How should I take JALYN?

- Take JALYN exactly as your healthcare provider tells you to take it.
- Swallow JALYN capsules whole. Do not crush, chew, or open JALYN capsules because the contents of the capsule may irritate your lips, mouth, or throat.
- Take your JALYN 1 time each day, about 30 minutes after the same meal every day. For example, you may take JALYN 30 minutes after dinner every day.
- If you miss a dose, you can take it later that same day, 30 minutes after a meal. Do not take 2 JALYN capsules in the same day. If you stop or forget to take JALYN for several days, talk with your healthcare provider before starting again.
- If you take too much JALYN, call your healthcare provider or go to the nearest hospital emergency room right away.

What should I avoid while taking JALYN?

- Avoid driving, operating machinery, or other dangerous activities when starting treatment with JALYN until you know how JALYN affects you. JALYN can cause a sudden drop in your blood pressure, especially at the start of treatment. A sudden drop in blood pressure may cause you to faint, feel dizzy or lightheaded.
- You should not donate blood while taking JALYN or for 6 months after you have stopped JALYN. This is important to prevent pregnant females from receiving JALYN through blood transfusions.

What are the possible side effects of JALYN?

JALYN may cause serious side effects including:

- Decreased blood pressure. JALYN may cause a sudden drop in your blood pressure upon standing from a sitting or lying position, especially at the start of treatment. Symptoms of low blood pressure may include:
  - fainting
  - dizziness
  - feeling lightheaded
- Rare and serious allergic reactions, including:
  - swelling of your face, tongue, or throat
  - difficulty breathing
  - serious skin reactions, such as skin peeling
  Get medical help right away if you have these serious allergic reactions.

Higher chance of a more serious form of prostate cancer.

- Eye problems during cataract or glaucoma surgery. During cataract or glaucoma surgery, a condition called Intraoperative Floppy Iris Syndrome (IFIS) can happen if you take or have taken JALYN in the past. If you need to have cataract or glaucoma surgery, tell your surgeon if you take or have taken JALYN.
- A painful erection that will not go away. Rarely, JALYN can cause a painful erection (priapism), which cannot be relieved by having sex. If this happens, get medical help right away. If priapism is not treated, there could be lasting damage to your penis, including not being able to have an erection.

The most common side effects of JALYN include:

- ejaculation problems [Some of these events may continue after you stop taking JALYN.]
- trouble getting or keeping an erection (impotence)
- a decrease in sex drive (libido)
- dizziness
- enlarged or painful breasts. If you notice breast lumps or nipple discharge, you should talk to your healthcare provider.
- runny nose

Depressed mood has been reported in patients receiving dutasteride, an ingredient of JALYN.

Dutasteride, an ingredient of JALYN, has been shown to reduce sperm count, semen volume, and sperm movement. However, the effect of JALYN on male fertility is not known.

Prostate-Specific Antigen (PSA) Test: Your healthcare provider may check you for other prostate problems, including prostate cancer before you start and while you take JALYN. A blood test called PSA (prostate-specific antigen) is sometimes used to see if you might have prostate cancer. JALYN will reduce the amount of PSA measured in your blood. Your healthcare provider is aware of this effect and can still use PSA to see if you might have prostate cancer. Increases in your PSA levels while on treatment with JALYN (even if the PSA levels are in the normal range) should be evaluated by your healthcare provider.

These are not all the possible side effects with JALYN. Call your doctor for medical advice about side effects. You may report side effects to FDA at 1-800-FDA-1088.

How should I store JALYN?

- Store JALYN capsules at room temperature (59° to 86°F or 15° to 30°C).
- JALYN capsules may become deformed and/or discolored if kept at high temperatures.
- Do not use or touch JALYN if your capsules are deformed, discolored, or leaking.
- Safety throw away medicines that is no longer needed.

Keep JALYN and all medicines out of the reach of children.

General information about the safe and effective use of JALYN.

Medicines are sometimes prescribed for purposes other than those listed in a Patient Information leaflet. Do not use Jalyn for a condition for which it was not prescribed. Do not give Jalyn to other people, even if they have the same symptoms that you have. It may harm them.

You can ask your healthcare provider or pharmacist for information about Jalyn that is written for health professionals.

For more information call 1-844-200-7910.

What are the ingredients in JALYN?

Active ingredient: dutasteride and tamsulosin hydrochloride

Inactive ingredients: black ink, butylated hydroxytoluene, carrageenan, FD&C yellow 6, ferric oxide (yellow), gelatin (from certified BSE-free bovine sources), glycerin, hypromellose, iron oxide red, methacrylic acid copolymer dispersion, microcrystalline cellulose, mono-di-glycerides of caprylic/capric acid, potassium chloride, talc, titanium dioxide, and triethyl citrate.

Manufactured for:
Waylis Therapeutics LLC
Rahway, NJ 07065

The other brand listed is a trademark owned by or licensed to its owner and is not owned by or licensed by Waylis Therapeutics LLC.

The maker of this brand is not affiliated with and does not endorse Waylis Therapeutics LLC or its products.

PRINCIPAL DISPLAY PANEL - 30 Capsule Bottle Label

NDC 80725-809-13
Waylis
THERAPEUTICS

Jalyn®
(dutasteride and tamsulosin HCl)
Capsules 0.5 mg / 0.4 mg

30 Capsules
Rx only

WARNING: JALYN should not be used by
women or children. Women who are or may
potentially be pregnant should not use or handle
JALYN Capsules (see prescribing information).
If contact is made with leaking capsule, wash
immediately with soap and water.

PRINCIPAL DISPLAY PANEL - 90 Capsule Bottle Label

NDC 80725-809-59
Waylis
THERAPEUTICS

Jalyn®
(dutasteride and tamsulosin HCl)
Capsules 0.5 mg / 0.4 mg

90 Capsules
Rx only

WARNING: JALYN should not be used by
women or children. Women who are or may
potentially be pregnant should not use or handle
JALYN Capsules (see prescribing information).
If contact is made with leaking capsule, wash
immediately with soap and water.